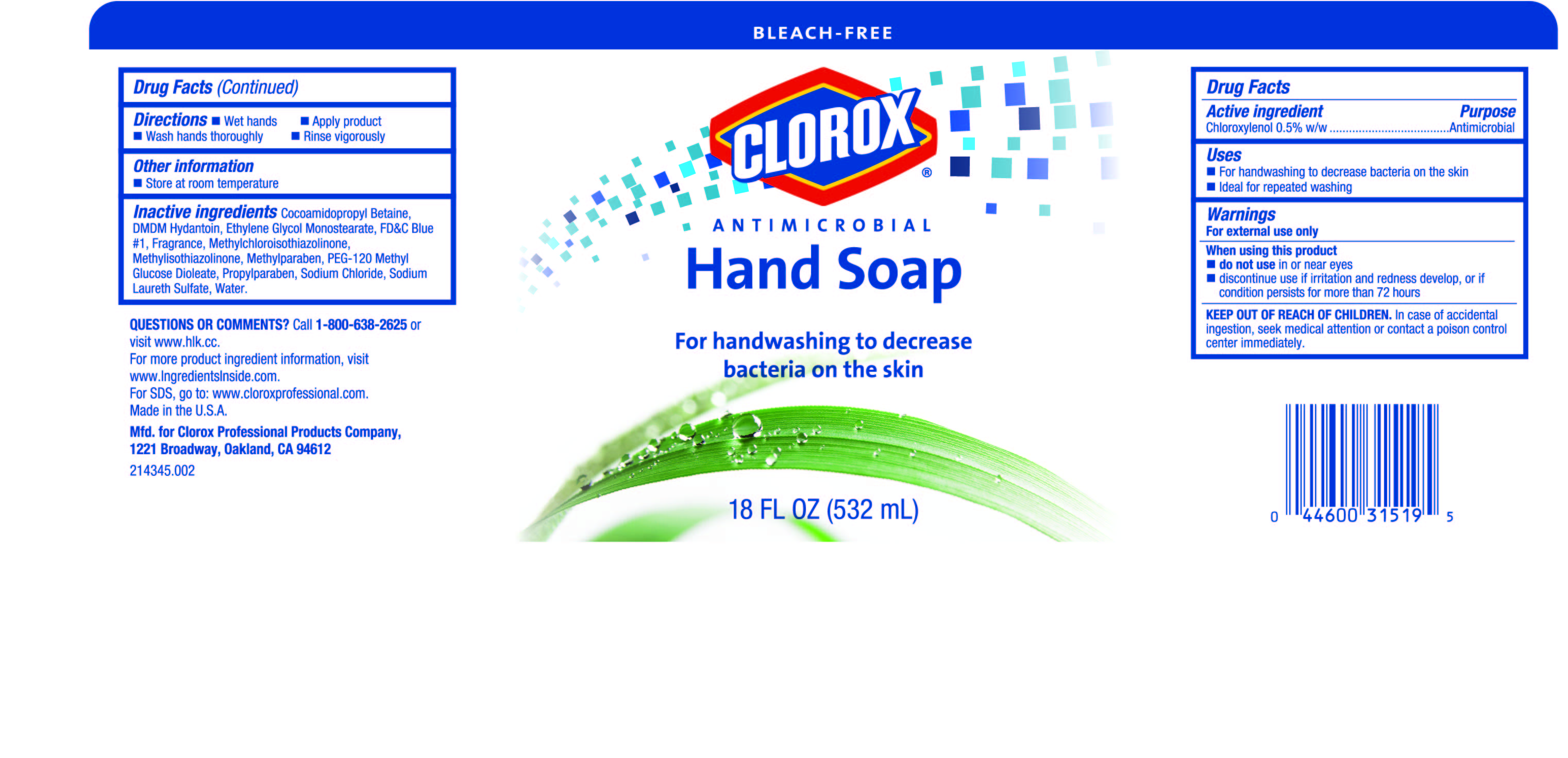 DRUG LABEL: Clorox Antimicrobial
NDC: 26509-0011 | Form: SOAP
Manufacturer: The Clorox Company
Category: otc | Type: HUMAN OTC DRUG LABEL
Date: 20160125

ACTIVE INGREDIENTS: CHLOROXYLENOL 5 mg/1 mL
INACTIVE INGREDIENTS: COCAMIDOPROPYL BETAINE; METHYLPARABEN; PEG-120 METHYL GLUCOSE DIOLEATE; PROPYLPARABEN; SODIUM CHLORIDE; GLYCOL STEARATE; SODIUM LAURETH-3 SULFATE; DMDM HYDANTOIN; FD&C BLUE NO. 1; METHYLCHLOROISOTHIAZOLINONE; WATER; METHYLISOTHIAZOLINONE

Active Ingredient

Chloroxylenol 0.5% w/w

Purpose

Antimicrobial

Uses

- For handwashing to decrease bacteria on the skin
- Ideal for repeated washing

Warnings

For external use only

When using this product

- do not use in or near eyes
- discontinue use if irritation and redness develop, or if condition persists for more than 72 hours

KEEP OUT OF REACH OF CHILDREN. In case of accidental ingestion, seek medical attention or contact a poison control center immediately.

Directions

- Wet hands
- Apply product
- Wash hands thoroughly
- Rinse vigorously

Other Information

Store at room temperature

INACTIVE INGREDIENT

Inactive IngredientsCocoamidopropyl Betaine, DMDM Hydantoin, Ethylene Glycol Monostearate, FD&C Blue #1, Fragrance, Methylchloroisothiazolinone, Methylisothiazolinone, Methylparaben, PEG-120 Methyl Glucose Dioleate, Propylparaben, Sodium Chloride, Sodium Laureth Sulfate, Water.

Questions or Comments?

Call 1-800-638-2625 or visit www.hlk.cc

PACKAGE LABEL

Clorox Antimicrobial Hand Soap

18 oz (532 mL)